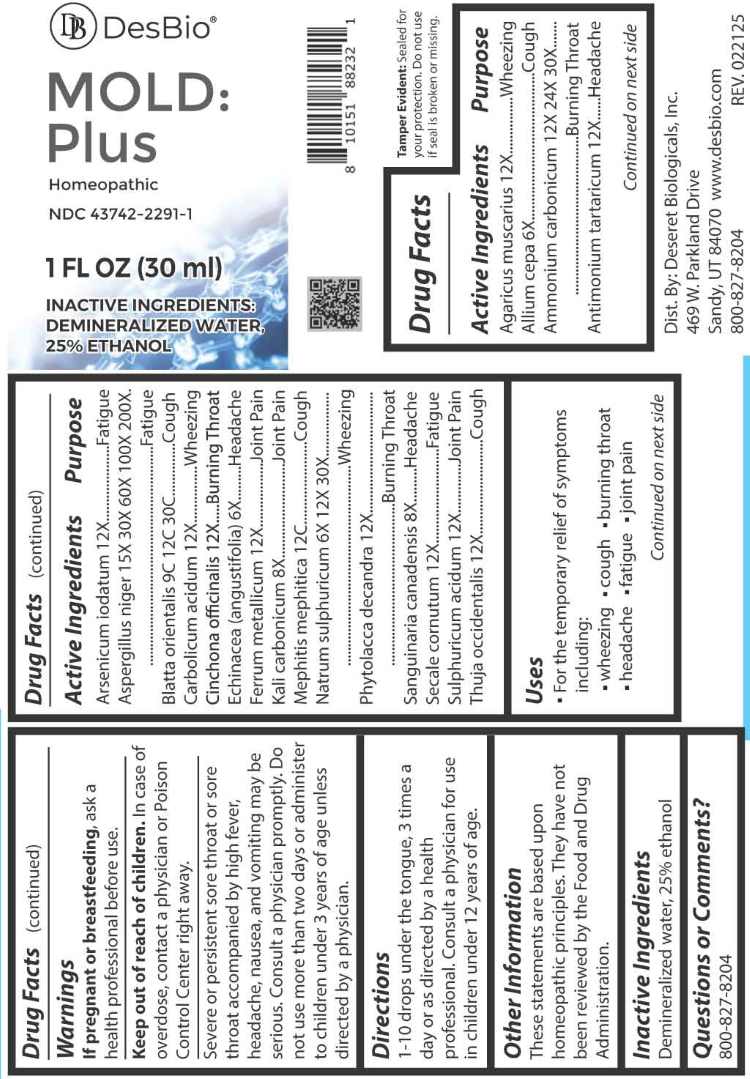 DRUG LABEL: Mold Plus
NDC: 43742-2291 | Form: LIQUID
Manufacturer: Deseret Biologicals, Inc.
Category: homeopathic | Type: HUMAN OTC DRUG LABEL
Date: 20260223

ACTIVE INGREDIENTS: AMANITA MUSCARIA FRUITING BODY 12 [hp_X]/1 mL; ONION 6 [hp_X]/1 mL; AMMONIUM CARBONATE 12 [hp_X]/1 mL; ANTIMONY POTASSIUM TARTRATE 12 [hp_X]/1 mL; ARSENIC TRIIODIDE 12 [hp_X]/1 mL; ASPERGILLUS NIGER VAR. NIGER 15 [hp_X]/1 mL; BLATTA ORIENTALIS 9 [hp_C]/1 mL; PHENOL 12 [hp_X]/1 mL; CINCHONA OFFICINALIS BARK 12 [hp_X]/1 mL; ECHINACEA ANGUSTIFOLIA WHOLE 6 [hp_X]/1 mL; IRON 12 [hp_X]/1 mL; POTASSIUM CARBONATE 8 [hp_X]/1 mL; MEPHITIS MEPHITIS ANAL GLAND FLUID 12 [hp_C]/1 mL; SODIUM SULFATE 6 [hp_X]/1 mL; PHYTOLACCA AMERICANA ROOT 12 [hp_X]/1 mL; SANGUINARIA CANADENSIS ROOT 8 [hp_X]/1 mL; CLAVICEPS PURPUREA SCLEROTIUM 12 [hp_X]/1 mL; SULFURIC ACID 12 [hp_X]/1 mL; THUJA OCCIDENTALIS LEAFY TWIG 12 [hp_X]/1 mL
INACTIVE INGREDIENTS: WATER; ALCOHOL

DRUG FACTS:

ACTIVE INGREDIENTS:

Agaricus Muscarius 12X, Allium Cepa 6X, Ammonium Carbonicum 12X, 24X, 30X, Antimonium Tartaricum 12X, Arsenicum Iodatum 12X, Aspergillus Niger 15X, 30X, 60X, 100X, 200X, Blatta Orientalis 9C, 12C, 30C, Carbolicum Acidum 12X, Cinchona Officinalis 12X, Echinacea (Angustifolia) 6X, Ferrum Metallicum 12X, Kali Carbonicum 8X, Mephitis Mephitica 12C, Natrum Sulphuricum 6X, 12X, 30X, Phytolacca Decandra 12X, Sanguinaria Canadensis 8X, Secale Cornutum 12X, Sulphuricum Acidum 12X, Thuja Occidentalis 12X.

PURPOSE:

Agaricus Muscarius - Wheezing, Allium Cepa - Cough, Ammonium Carbonicum – Burning Throat, Antimonium Tartaricum - Headache, Arsenicum Iodatum - Fatigue, Aspergillus Niger - Fatigue, Blatta Orientalis - Cough, Carbolicum Acidum - Wheezing, Cinchona Officinalis – Burning Throat, Echinacea (Angustifolia) - Headache, Ferrum Metallicum – Joint Pain, Kali Carbonicum – Joint Pain, Mephitis Mephitica - Cough, Natrum Sulphuricum - Wheezing, Phytolacca Decandra – Burning Throat, Sanguinaria Canadensis - Headache, Secale Cornutum - Fatigue, Sulphuricum Acidum – Joint Pain, Thuja Occidentalis – Thuja Occidentalis

USES:

• For the temporary relief of symptoms including:

• wheezing • cough • burning throat • headache • fatigue • joint pain

These statements are based upon homeopathic principles. They have not been reviewed by the Food and Drug Administration.

WARNINGS:

If pregnant or breastfeeding, ask a health professional before use.

Keep out of reach of children. In case of overdose, contact a physician or Poison Control Center right away.

Severe or persistent sore throat or sore throat accompanied by high fever, headache, nausea, and vomiting may be serious. Consult a physician promptly. Do not use more than two days or administer to children under 3 years of age unless directed by a physician.

Tamper Evident: Sealed for your protection. Do not use if seal is broken or missing.

KEEP OUT OF REACH OF CHILDREN:

In case of overdose, contact a physician or Poison Control Center right away.

DIRECTIONS:

1-10 drops under the tongue, 3 times a day or as directed by a health professional. Consult a physician for use in children under 12 years of age.

INACTIVE INGREDIENTS:

Demineralized water, 25% ethanol

QUESTIONS:

Dist. By: Deseret Biologicals, Inc.

469 W. Parkland Drive

Sandy, UT 84070

www.desbio.com

800-827-8204

PACKAGE LABEL DISPLAY:

DesBio

MOLD: Plus

Homeopathic

NDC 43742-2291-1

1 FL OZ (30ml)